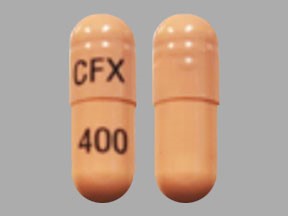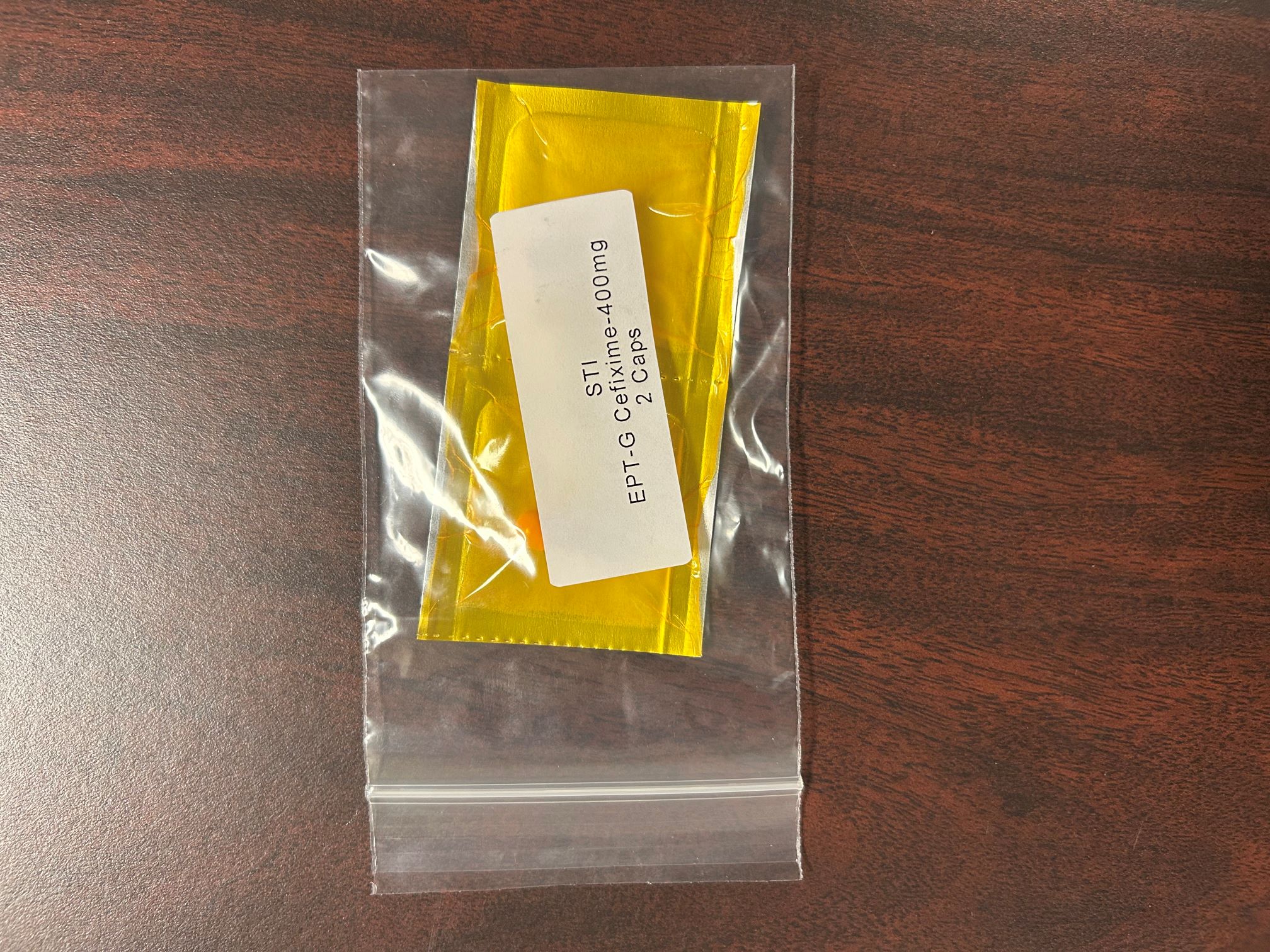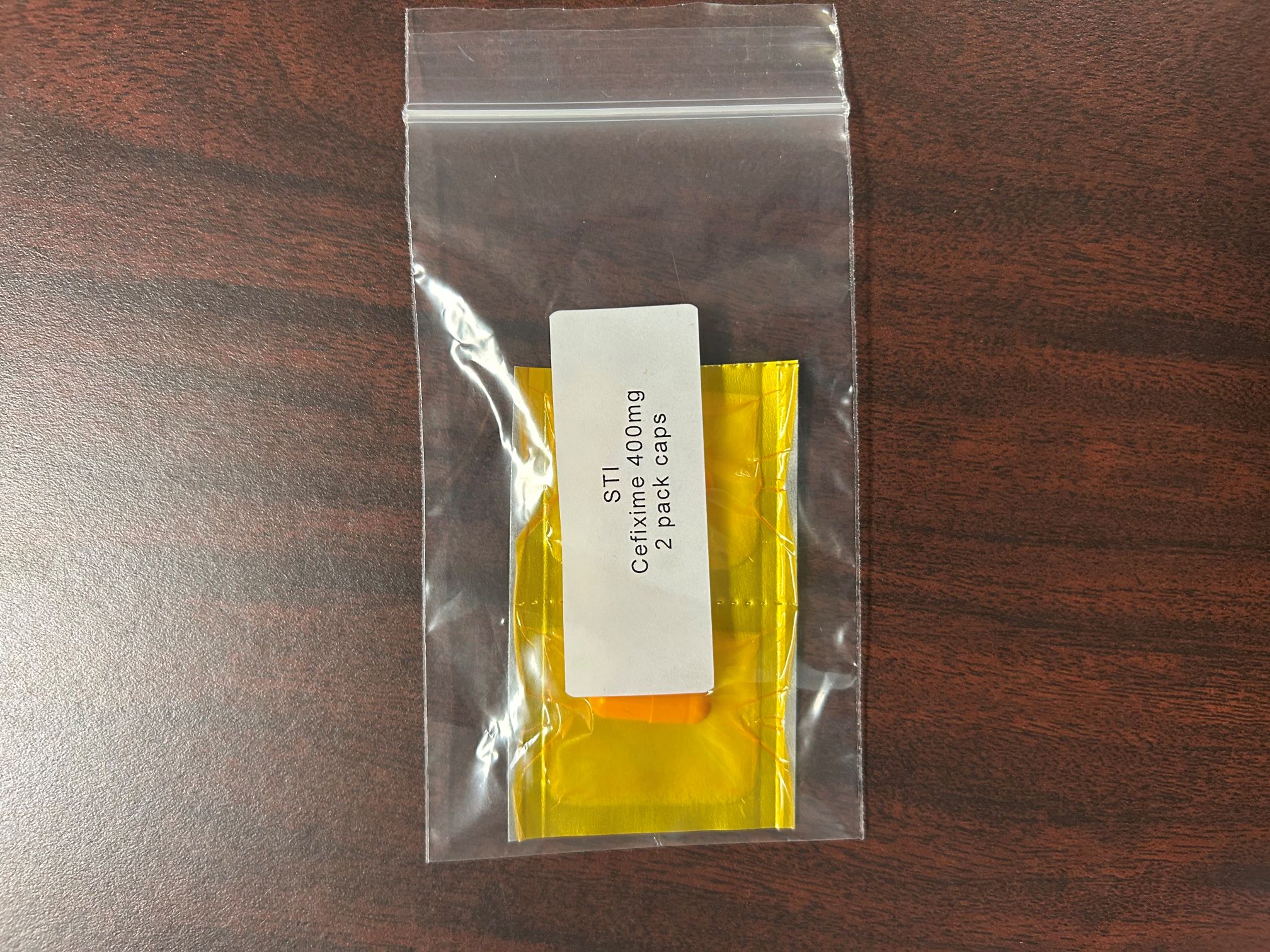 DRUG LABEL: Cefixime 400 mg
NDC: 83112-400 | Form: CAPSULE
Manufacturer: Health Department, Oklahoma State
Category: prescription | Type: HUMAN PRESCRIPTION DRUG LABEL
Date: 20251220

ACTIVE INGREDIENTS: CEFIXIME 400 mg/1 1

Cefixime 400 mg UD

WARNINGS AND PRECAUTIONS

5.1 Hypersensitivity Reactions

Anaphylactic/anaphylactoid reactions (including shock and fatalities) have been reported with the use of cefixime.

Before therapy with cefixime is instituted, careful inquiry should be made to determine whether the patient has had previous hypersensitivity reactions to cephalosporins, penicillins, or other drugs. If this product is to be given to penicillin-sensitive patients, caution should be exercised because cross hypersensitivity among beta-lactam antibiotics has been clearly documented and may occur in up to 10% of patients with a history of penicillin allergy. If an allergic reaction to cefixime occurs, discontinue the drug.

5.2 Clostridium difficile-Associated Diarrhea

Clostridium difficile associated diarrhea (CDAD) has been reported with use of nearly all antibacterial agents, including cefixime, and may range in severity from mild diarrhea to fatal colitis. Treatment with antibacterial agents alters the normal flora of the colon leading to overgrowth of C. difficile.

C. difficile produces toxins A and B which contribute to the development of CDAD. Hypertoxin producing isolates of C. difficile cause increased morbidity and mortality, as these infections can be refractory to antimicrobial therapy and may require colectomy. CDAD must be considered in all patients who present with diarrhea following antibacterial use. Careful medical history is necessary since CDAD has been reported to occur over two months after the administration of antibacterial agents.

If CDAD is suspected or confirmed, ongoing antibacterial use not directed against C. difficile may need to be discontinued. Appropriate fluid and electrolyte management, protein supplementation, antibacterial treatment of C. difficile, and surgical evaluation should be instituted as clinically indicated.

5.3 Dose Adjustment in Renal Impairment

The dose of cefixime should be adjusted in patients with renal impairment as well as those undergoing continuous ambulatory peritoneal dialysis (CAPD) and hemodialysis (HD). Patients on dialysis should be monitored carefully [see DOSAGE AND ADMINISTRATION (2)].

5.4 Coagulation Effects

Cephalosporins, including cefixime, may be associated with a fall in prothrombin activity. Those at risk include patients with renal or hepatic impairment, or poor nutritional state, as well as patients receiving a protracted course of antimicrobial therapy, and patients previously stabilized on anticoagulant therapy. Prothrombin time should be monitored in patients at risk and exogenous vitamin K administered as indicated.

5.5 Development of Drug-Resistant Bacteria

Prescribing cefixime in the absence of a proven or strongly suspected bacterial infection is unlikely to provide benefit to the patient and increases the risk of the development of drug-resistant bacteria.